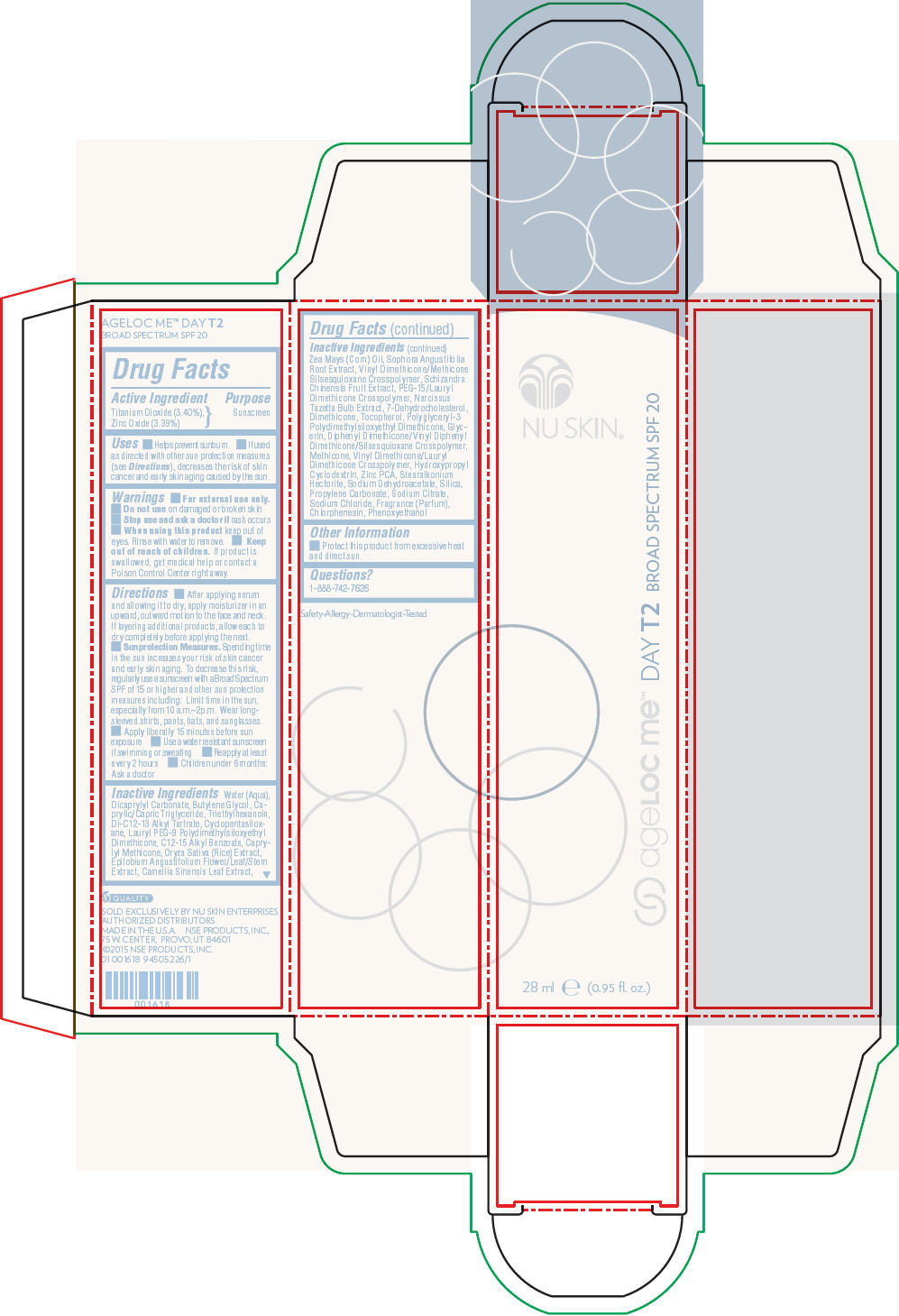 DRUG LABEL: Nu Skin ageLOC Me Day T2 Broad Spectrum SPF 20
NDC: 62839-1618 | Form: LOTION
Manufacturer: NSE Products, Inc.
Category: otc | Type: HUMAN OTC DRUG LABEL
Date: 20191226

ACTIVE INGREDIENTS: Titanium Dioxide 34 mg/1 mL; Zinc Oxide 33.9 mg/1 mL
INACTIVE INGREDIENTS: Water; Dicaprylyl Carbonate; Butylene Glycol; Medium-Chain Triglycerides; Triethylhexanoin; Di-C12-13 Alkyl Tartrate; Cyclomethicone 5; Lauryl PEG-9 Polydimethylsiloxyethyl Dimethicone; Alkyl (C12-15) Benzoate; Caprylyl Trisiloxane; Phenoxyethanol; Silicon Dioxide; Sodium Chloride; Glycerin; Rice Germ; Stearalkonium Hectorite; Chlorphenesin; Sodium Citrate, Unspecified Form; Zinc Pidolate; Dimethicone; Propylene Carbonate; Sodium Dehydroacetate; Sophora Flavescens Root; Green Tea Leaf; Schisandra Chinensis Fruit; Corn Oil; Epilobium Angustifolium Flowering Top; Narcissus Tazetta Bulb; 7-Dehydrocholesterol; Tocopherol

Nu Skin® ageLOC Me™ Day T2 Broad Spectrum SPF 20

Drug Facts

Active Ingredient

Titanium Dioxide (3.40%),
Zinc Oxide (3.39%)

Purpose

Sunscreen

Uses

- Helps prevent sunburn.
- If used as directed with other sun protection measures (see Directions), decreases the risk of skin cancer and early skin aging caused by the sun.

Warnings

- For external use only.

- Do not use on damaged or broken skin

- Stop use and ask a doctor if rash occurs

- When using this product keep out of eyes. Rinse with water to remove.

- Keep out of reach of children. If product is swallowed, get medical help or contact a Poison Control Center right away.

Directions

- After applying serum and allowing it to dry, apply moisturizer in an upward, outward motion to the face and neck. If layering additional products, allow each to dry completely before applying the next.
- Sunprotection Measures. Spending time in the sun increases your risk of skin cancer and early skin aging. To decrease this risk, regularly use a sunscreen with a Broad Spectrum SPF of 15 or higher and other sun protection measures including: Limit time in the sun, especially from 10 a.m.–2p.m. Wear long-sleeved shirts, pants, hats, and sunglasses.
- Apply liberally 15 minutes before sun exposure
- Use a water resistant sunscreen if swimming or sweating
- Reapply at least every 2 hours
- Children under 6 months: Ask a doctor

Inactive Ingredients

Water (Aqua), Dicaprylyl Carbonate, Butylene Glycol, Caprylic/Capric Triglyceride, Triethylhexanoin, Di-C12-13 Alkyl Tartrate, Cyclopentasiloxane, Lauryl PEG-9 Polydimethylsiloxyethyl Dimethicone, C12-15 Alkyl Benzoate, Caprylyl Methicone, Oryza Sativa (Rice) Extract, Epilobium Angustifolium Flower/Leaf/Stem Extract, Camellia Sinensis Leaf Extract, Zea Mays (Corn) Oil, Sophora Angustifolia Root Extract, Vinyl Dimethicone/Methicone Silsesquioxane Crosspolymer, Schizandra Chinensis Fruit Extract, PEG-15/Lauryl Dimethicone Crosspolymer, Narcissus Tazetta Bulb Extract, 7-Dehydrocholesterol, Dimethicone, Tocopherol, Polyglyceryl-3 Polydimethylsiloxyethyl Dimethicone, Glycerin, Diphenyl Dimethicone/Vinyl Diphenyl Dimethicone/Silsesquioxane Crosspolymer, Methicone, Vinyl Dimethicone/Lauryl Dimethicone Crosspolymer, Hydroxypropyl Cyclodextrin, Zinc PCA, Stearalkonium Hectorite, Sodium Dehydroacetate, Silica, Propylene Carbonate, Sodium Citrate, Sodium Chloride, Fragrance (Parfum), Chlorphenesin, Phenoxyethanol

Other Information

- Protect this product from excessive heat and direct sun.

Questions?

1-888-742-7626

PRINCIPAL DISPLAY PANEL - 28 ml Cartridge Carton

NU SKIN®

ageLOC me™ DAY T2 BROAD SPECTRUM SPF 20

28 ml e (0.95 fl. oz.)